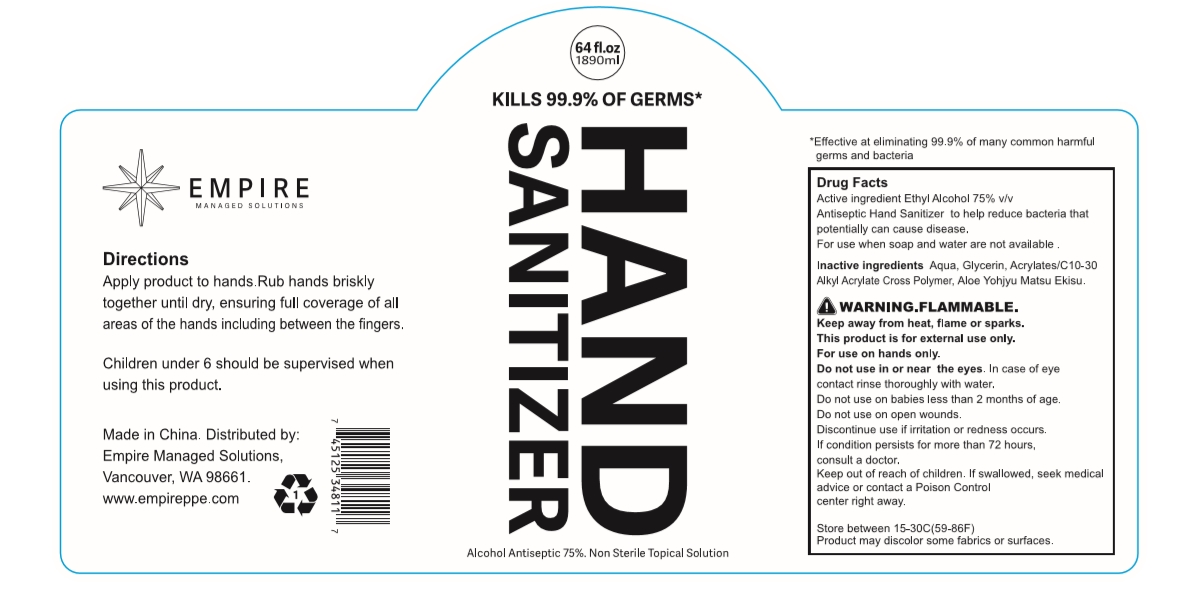 DRUG LABEL: Hand Sanitizer
NDC: 54237-020 | Form: LIQUID
Manufacturer: Guangzhou Daieme Cosmetic Co,.Ltd
Category: otc | Type: HUMAN OTC DRUG LABEL
Date: 20230309

ACTIVE INGREDIENTS: ALCOHOL 1417.5 mL/1890 mL
INACTIVE INGREDIENTS: ALOE; GLYCERIN; CARBOMER INTERPOLYMER TYPE A (55000 CPS); WATER

DOSAGE AND ADMINISTRATION

Store between 15-30°C(59-86°F)

ACTIVE INGREDIENT

Ethyl Alcohol

keep out of reach of children

WARNINGS

Alcohol is volatile ,Please use it as so0n as possible after opening.Place it in a cool and dry place, avoid direct sunlight and fire,and avoid children eating by mistake.Please keep out of the reach of children,Avold contact with eyes and damaged skin.

INACTIVE INGREDIENT

Aqua, Glycerin, Acrylates/C10-30 Alkyl Acrylate Cross Polymer, Aloe Extract

PURPOSE

Disinfection
Sterilization
No Rinseing

INDICATIONS AND USAGE

open the label, Take out the wet towel and use.